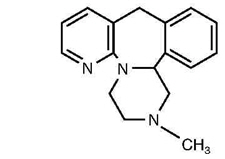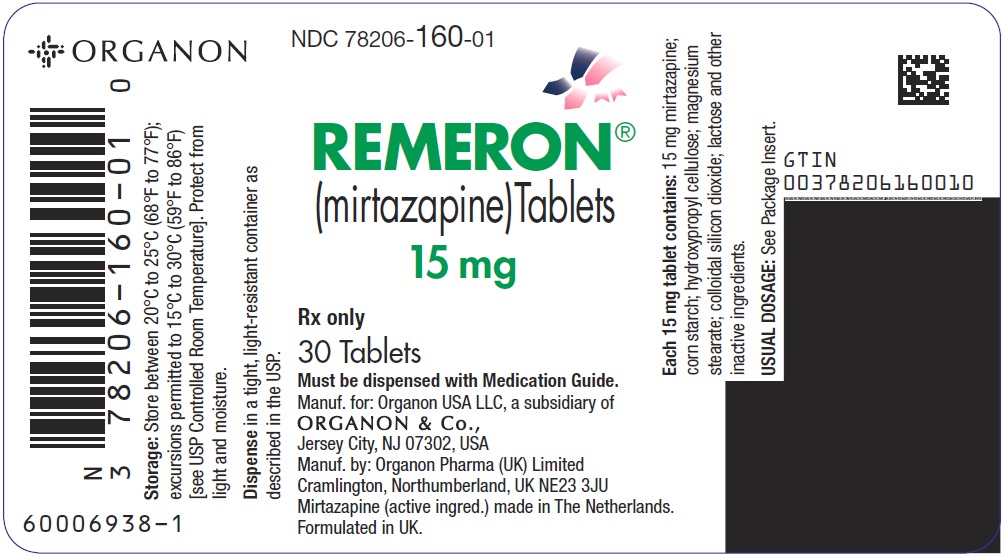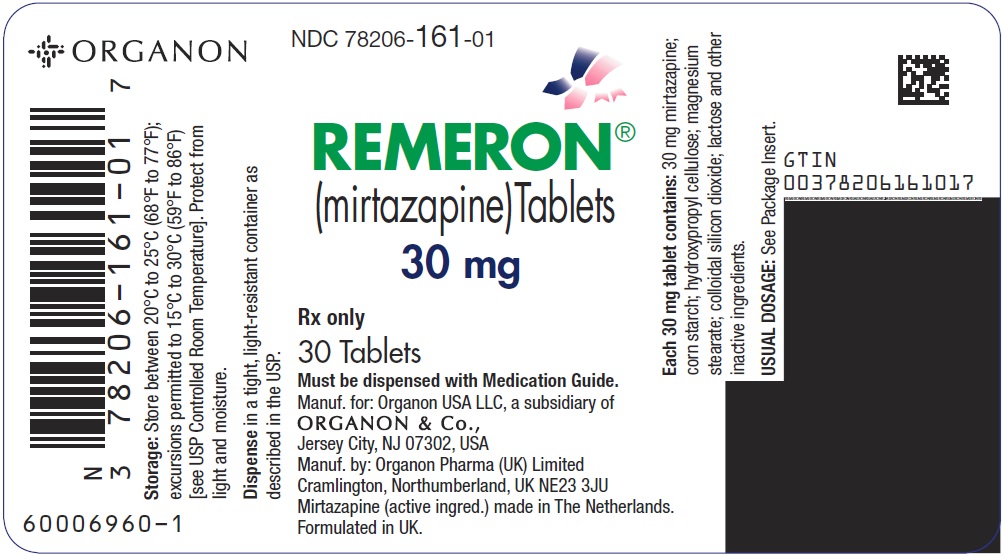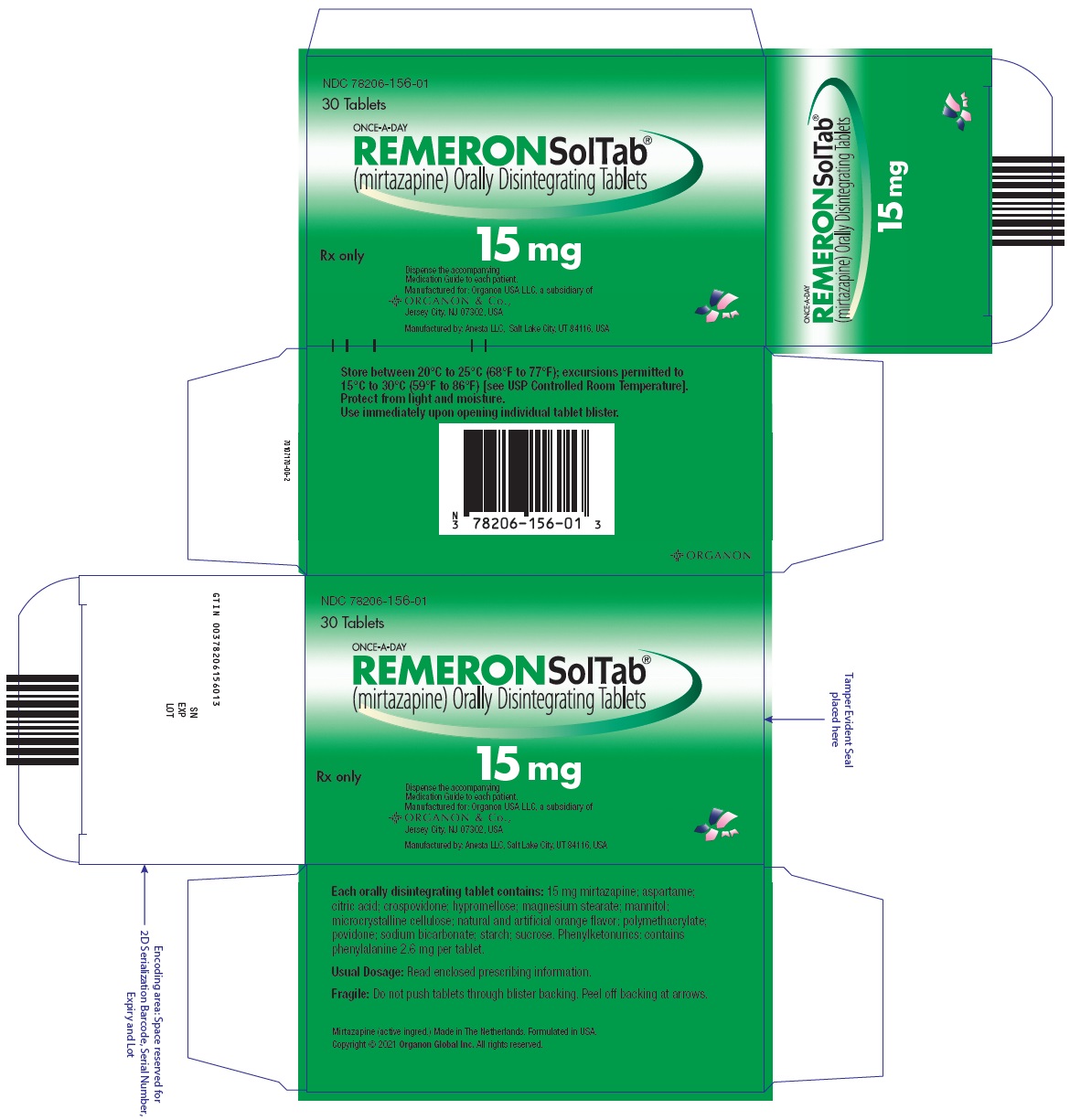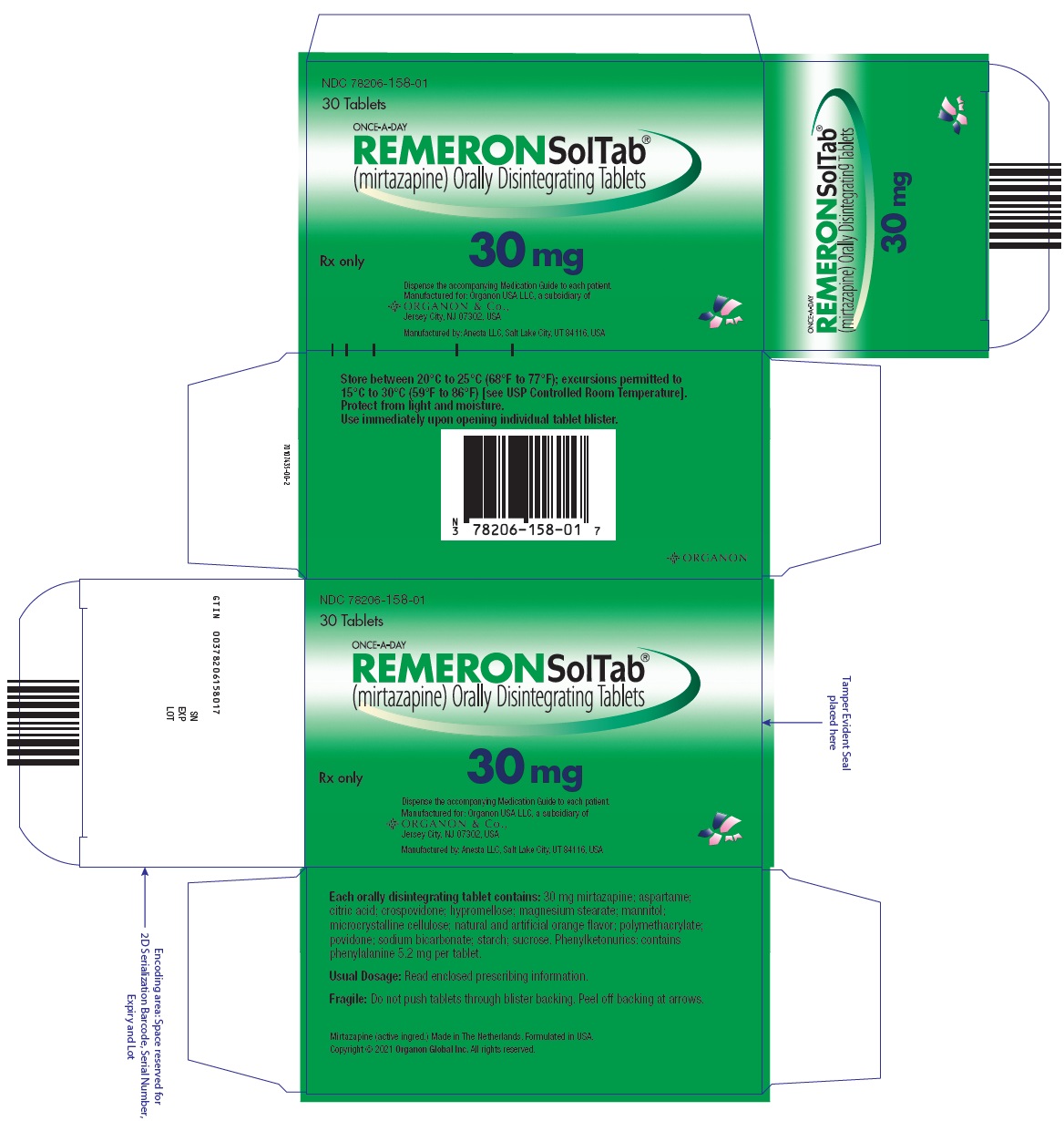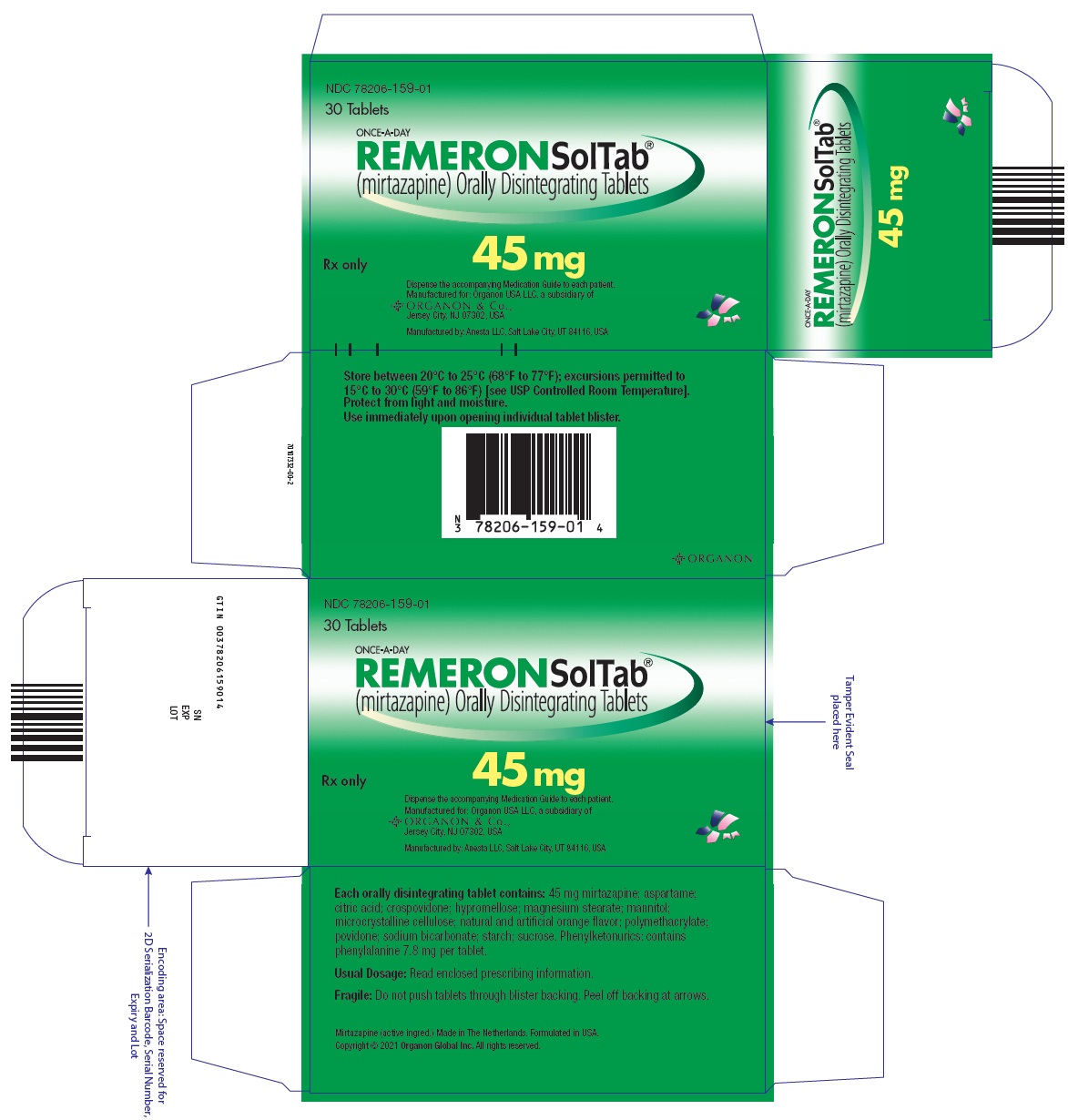 DRUG LABEL: REMERON
NDC: 78206-160 | Form: TABLET, FILM COATED
Manufacturer: Organon LLC
Category: prescription | Type: HUMAN PRESCRIPTION DRUG LABEL
Date: 20250806

ACTIVE INGREDIENTS: MIRTAZAPINE 15 mg/1 1
INACTIVE INGREDIENTS: STARCH, CORN; HYDROXYPROPYL CELLULOSE (1600000 WAMW); MAGNESIUM STEARATE; SILICON DIOXIDE; LACTOSE, UNSPECIFIED FORM; HYPROMELLOSE, UNSPECIFIED; POLYETHYLENE GLYCOL 8000; TITANIUM DIOXIDE; FERRIC OXIDE YELLOW

HIGHLIGHTS OF PRESCRIBING INFORMATION

These highlights do not include all the information needed to use REMERON/REMERONSolTab safely and effectively. See full prescribing information for REMERON/REMERONSolTab.
REMERON® (mirtazapine) tablets, for oral use
REMERONSolTab® (mirtazapine) orally disintegrating tablets
Initial U.S. Approval: 1996

RECENT MAJOR CHANGES

Contraindications (4) | 11/2021
Warnings and Precautions (5.6) | 11/2021

WARNING: SUICIDAL THOUGHTS AND BEHAVIORS

See full prescribing information for complete boxed warning.

Increased risk of suicidal thoughts and behavior in pediatric and young adult patients taking antidepressants. Closely monitor all antidepressant-treated patients for clinical worsening and emergence of suicidal thoughts and behaviors. REMERON/REMERONSolTab is not approved for use in pediatric patients. (5.1, 8.4)

1 INDICATIONS AND USAGE

REMERON/REMERONSolTab is indicated for the treatment of major depressive disorder (MDD) in adults. (1)

2 DOSAGE AND ADMINISTRATION

- Starting dose: 15-mg once daily; may increase up to maximum recommended dose of 45 mg once daily. (2.1)
- Administer orally once daily, preferably in the evening prior to sleep. (2.1)
- Administer REMERONSolTab immediately after removal from blister pack. (2.2)
- Reduce dose gradually when discontinuing REMERON/REMERONSolTab. (2.6, 5.14)

3 DOSAGE FORMS AND STRENGTHS

- Tablets: 15 mg scored and 30 mg scored. (3)
- Orally disintegrating tablets: 15 mg, 30 mg, and 45 mg. (3)

4 CONTRAINDICATIONS

- Concomitant use of monoamine oxidase inhibitors (MAOIs) or use within 14 days of stopping MAOIs. (2.4, 4, 7)
- Known hypersensitivity to mirtazapine or any of the excipients in REMERON/REMERONSolTab. (4)

5 WARNINGS AND PRECAUTIONS

- Agranulocytosis: If sore throat, fever, stomatitis or signs of infection occur, along with a low white blood cell count, treatment with REMERON/REMERONSolTab should be discontinued and the patient should be closely monitored. (5.2)
- Serotonin Syndrome: Increased risk when co-administered with other serotonergic drugs (e.g., SSRI, SNRI, triptans), but also when taken alone. If it occurs, discontinue REMERON/REMERONSolTab and initiate supportive treatment. (2.4, 4, 5.3, 7)
- Angle-Closure Glaucoma: Angle closure glaucoma has occurred in patients with untreated anatomically narrow angles treated with antidepressants. (5.4)
- QT Prolongation: Use REMERON/REMERONSolTab with caution in patients with risk factors for QT prolongation. (5.5, 7)
- Drug Reaction with Eosinophilia and System Symptoms (DRESS): Discontinue REMERON/REMERONSolTab if DRESS is suspected. (5.6)
- Increased Appetite/Weight Gain: REMERON/REMERONSolTab has been associated with increased appetite and weight gain. (5.7)
- Somnolence: May impair judgment, thinking and/or motor skills. Use with caution when engaging in activities requiring alertness, such as driving or operating machinery. (5.8, 7)
- Activation of Mania/Hypomania: Screen patients for bipolar disorder prior to initiating treatment. (2.3, 5.9)
- Seizures: Use with caution in patients with a seizure disorder. (5.10)
- Elevated Cholesterol/Triglycerides: Has been reported with REMERON use. (5.11)
- Hyponatremia: May occur as a result of treatment with serotonergic antidepressants, including REMERON/REMERONSolTab. (5.12)
- Transaminase Elevations: Clinically significant elevations have occurred. Use with caution in patients with impaired hepatic function. (5.13)

6 ADVERSE REACTIONS

Most common adverse reactions (≥5% or greater and twice placebo) were somnolence, increased appetite, weight gain, and dizziness. (6.1)

To report SUSPECTED ADVERSE REACTIONS, contact Organon USA LLC, a subsidiary of Organon & Co., at 1-844-674-3200 or FDA at 1-800-FDA-1088 or www.fda.gov/medwatch.

7 DRUG INTERACTIONS

- Strong CYP3A inducers: Dosage increase may be needed for REMERON/REMERONSolTab with concomitant use of strong CYP3A inducers. (2.5, 7)
- Strong CYP3A inhibitors: Dosage decrease may be needed when REMERON/REMERONSolTab is coadministered with strong CYP3A inhibitors. (2.5, 7)
- Cimetidine: Dosage decrease may be needed when REMERON/REMERONSolTab is coadministered with cimetidine. (2.5, 7)
- Warfarin: Monitor INR during concomitant use. (7)

8 USE IN SPECIFIC POPULATIONS

- Geriatric Use: Use with caution in elderly patients. (5.12, 5.15, 8.5)
- Renal impairment: Dosage decrease may be needed in patients with moderate to severe renal impairment. (8.6)
- Hepatic impairment: Dosage decrease may be needed in patients with hepatic impairment. (8.6)
- Patients with Phenylketonuria: REMERONSolTab contains phenylalanine. (5.16, 8.7)

FULL PRESCRIBING INFORMATION

WARNING: SUICIDAL THOUGHTS AND BEHAVIORS

Antidepressants increased the risk of suicidal thoughts and behaviors in pediatric and young adult patients in short-term studies. Closely monitor all antidepressant-treated patients for clinical worsening, and for emergence of suicidal thoughts and behaviors [see Warnings and Precautions (5.1)]. REMERON/REMERONSolTab is not approved for use in pediatric patients [see Use in Specific Populations (8.4)].

1 INDICATIONS AND USAGE

REMERON/REMERONSolTab are indicated for the treatment of major depressive disorder (MDD) in adults [see Clinical Studies (14)].

2 DOSAGE AND ADMINISTRATION

2.1 Recommended Dosage

The recommended starting dose of REMERON/REMERONSolTab is 15 mg once daily, administered orally, preferably in the evening prior to sleep. If patients do not have an adequate response to the initial 15 mg dose, increase the dose up to a maximum of 45 mg per day. Dose changes should not be made in intervals of less than 1 to 2 weeks to allow sufficient time for evaluation of response to a given dose [see Clinical Pharmacology (12.3)].

2.2 Administration of REMERONSolTab

- The tablet should remain in the blister pack until the patient is ready to take it.
- The patient or caregiver should use dry hands to open the blister.
- As soon as the blister is opened, the tablet should be removed and placed on the patient's tongue.
- Use REMERONSolTab immediately after removal from its blister; once removed, it cannot be stored.
- The whole tablet should be placed on the tongue and allowed to disintegrate without chewing or crushing. Do not attempt to split the tablet.
- The tablet will disintegrate in saliva so that it can be swallowed.

2.3 Screen for Bipolar Disorder Prior to Starting REMERON/REMERONSolTab

Prior to initiating treatment with REMERON/REMERONSolTab or another antidepressant, screen patients for a personal or family history of bipolar disorder, mania, or hypomania [see Warnings and Precautions (5.9)].

2.4 Switching Patients to or from a Monoamine Oxidase Inhibitor Antidepressant

At least 14 days must elapse between discontinuation of a monoamine oxidase inhibitor (MAOI) antidepressant and initiation of REMERON/REMERONSolTab. In addition, at least 14 days must elapse after stopping REMERON/REMERONSolTab before starting an MAOI antidepressant [see Contraindications (4) and Warnings and Precautions (5.3)].

2.5 Dosage Modifications Due to Drug Interactions

Strong CYP3A Inducers

An increase in dosage of REMERON/REMERONSolTab may be needed with concomitant strong CYP3A inducer (e.g., carbamazepine, phenytoin, rifampin) use. Conversely, a decrease in dosage of REMERON/REMERONSolTab may be needed if the CYP3A inducer is discontinued [see Drug Interactions (7)].

Strong CYP3A Inhibitors

A decrease in dosage of REMERON/REMERONSolTab may be needed with concomitant use of strong CYP3A4 inhibitors (e.g., ketoconazole, clarithromycin). Conversely, an increase in dosage of REMERON/REMERONSolTab may be needed if the CYP3A4 inhibitor is discontinued [see Drug Interactions (7)].

Cimetidine

A decrease in dosage of REMERON/REMERONSolTab may be needed with concomitant use of cimetidine. Conversely, an increase in dosage of REMERON/REMERONSolTab may be needed if cimetidine is discontinued [see Drug Interactions (7)].

2.6 Discontinuation of REMERON/REMERONSolTab Treatment

Adverse reactions may occur upon discontinuation or dose reduction of REMERON/REMERONSolTab [see Warnings and Precautions (5.14)]. Gradually reduce the dosage of REMERON/REMERONSolTab rather than stopping abruptly whenever possible.

3 DOSAGE FORMS AND STRENGTHS

REMERON is supplied as:

- 15 mg tablets: Oval, scored, yellow, with "MSD" debossed on one side and "T3Z" on the other side, on both sides of the score line
- 30 mg tablets: Oval, scored, red-brown, with "MSD" debossed on one side and "T5Z" on the other side, on both sides of the score line

REMERONSolTab is supplied as:

- 15 mg orally disintegrating tablets: Round, white, with "T1Z" debossed on one side
- 30 mg orally disintegrating tablets: Round, white, with "T2Z" debossed on one side
- 45 mg orally disintegrating tablets: Round, white, with "T4Z" debossed on one side

4 CONTRAINDICATIONS

REMERON/REMERONSolTab is contraindicated in patients:

- Taking, or within 14 days of stopping, MAOIs (including the MAOIs linezolid and intravenous methylene blue) because of an increased risk of serotonin syndrome [see Warnings and Precautions (5.3), Drug Interactions (7)].
- With a known hypersensitivity to mirtazapine or to any of the excipients in REMERON/REMERONSolTab. Severe skin reactions, including drug reaction with eosinophilia and systemic symptoms (DRESS), Stevens-Johnson syndrome, bullous dermatitis, erythema multiforme and toxic epidermal necrolysis have been reported following the use of REMERON/REMERONSolTab [see Warnings and Precautions (5.6), Adverse Reactions (6.2)].

5 WARNINGS AND PRECAUTIONS

5.1 Suicidal Thoughts and Behaviors in Adolescents and Young Adults

In pooled analyses of placebo-controlled trials of antidepressant drugs (SSRIs and other antidepressant classes) that included approximately 77,000 adult patients and 4,500 pediatric patients, the incidence of suicidal thoughts and behaviors in antidepressant-treated patients age 24 years and younger was greater than in placebo-treated patients. There was considerable variation in risk of suicidal thoughts and behaviors among drugs, but there was an increased risk identified in young patients for most drugs studied. There were differences in absolute risk of suicidal thoughts and behaviors across the different indications, with the highest incidence in patients with MDD. The drug-placebo differences in the number of cases of suicidal thoughts and behaviors per 1000 patients treated are provided in Table 1.

Table 1: Risk Differences of the Number of Patients with Suicidal Thoughts and Behavior in the Pooled Placebo-Controlled Trials of Antidepressants in Pediatric and Adult Patients
Age Range | Drug-Placebo Difference in Number of Patients with Suicidal Thoughts or Behaviors per 1000 Patients Treated
 | Increases Compared to Placebo
<18 years old | 14 additional patients
18–24 years old | 5 additional patients
 | Decreases Compared to Placebo
25–64 years old | 1 fewer patient
≥65 years old | 6 fewer patients

It is unknown whether the risk of suicidal thoughts and behaviors in children, adolescents, and young adults extends to longer-term use, i.e., beyond four months. However, there is substantial evidence from placebo-controlled maintenance trials in adults with MDD that antidepressants delay the recurrence of depression and that depression itself is a risk factor for suicidal thoughts and behaviors.

Monitor all antidepressant-treated patients for any indication of clinical worsening and emergence of suicidal thoughts and behaviors, especially during the initial few months of drug therapy, and at times of dosage changes. Counsel family members or caregivers of patients to monitor for changes in behavior and to alert the healthcare provider. Consider changing the therapeutic regimen, including possibly discontinuing REMERON/REMERONSolTab, in patients whose depression is persistently worse, or who are experiencing emergent suicidal thoughts or behaviors.

5.2 Agranulocytosis

In premarketing clinical trials, 2 (1 with Sjögren's Syndrome) out of 2796 patients treated with REMERON developed agranulocytosis [absolute neutrophil count (ANC) <500/mm^3 with associated signs and symptoms, e.g., fever, infection, etc.] and a third patient developed severe neutropenia (ANC <500/mm^3 without any associated symptoms). For these 3 patients, onset of severe neutropenia was detected on days 61, 9, and 14 of treatment, respectively. All 3 patients recovered after REMERON was stopped. If a patient develops a sore throat, fever, stomatitis, or other signs of infection, along with a low white blood cell (WBC) count, treatment with REMERON/REMERONSolTab should be discontinued and the patient should be closely monitored.

5.3 Serotonin Syndrome

Serotonergic antidepressants, including REMERON/REMERONSolTab, can precipitate serotonin syndrome, a potentially life-threatening condition. The risk is increased with concomitant use of other serotonergic drugs (including triptans, tricyclic antidepressants, fentanyl, lithium, tramadol, tryptophan, buspirone, amphetamines, and St. John's Wort) and with drugs that impair metabolism of serotonin, i.e., MAOIs [see Contraindications (4), Drug Interactions (7)]. Serotonin syndrome can also occur when these drugs are used alone.

Serotonin syndrome signs and symptoms may include mental status changes (e.g., agitation, hallucinations, delirium, and coma), autonomic instability (e.g., tachycardia, labile blood pressure, dizziness, diaphoresis, flushing, hyperthermia), neuromuscular symptoms (e.g., tremor, rigidity, myoclonus, hyperreflexia, incoordination), seizures, and gastrointestinal symptoms (e.g., nausea, vomiting, diarrhea).

The concomitant use of REMERON/REMERONSolTab with MAOIs is contraindicated. In addition, do not initiate REMERON/REMERONSolTab in a patient being treated with MAOIs such as linezolid or intravenous methylene blue. No reports involved the administration of methylene blue by other routes (such as oral tablets or local tissue injection). If it is necessary to initiate treatment with an MAOI such as linezolid or intravenous methylene blue in a patient taking REMERON/REMERONSolTab, discontinue REMERON/REMERONSolTab before initiating treatment with the MAOI [see Contraindications (4), Drug Interactions (7)].

Monitor all patients taking REMERON/REMERONSolTab for the emergence of serotonin syndrome. Discontinue treatment with REMERON/REMERONSolTab and any concomitant serotonergic agents immediately if the above symptoms occur, and initiate supportive symptomatic treatment. If concomitant use of REMERON/REMERONSolTab with other serotonergic drugs is clinically warranted, inform patients of the increased risk for serotonin syndrome and monitor for symptoms.

5.4 Angle-Closure Glaucoma

The pupillary dilation that occurs following use of many antidepressant drugs, including REMERON/REMERONSolTab, may trigger an angle-closure attack in a patient with anatomically narrow angles who does not have a patent iridectomy.

5.5 QT Prolongation and Torsades de Pointes

The effect of REMERON (mirtazapine) on QTc interval was assessed in a clinical randomized trial with placebo and positive (moxifloxacin) controls involving 54 healthy volunteers using exposure response analysis. This trial showed a positive relationship between mirtazapine concentrations and prolongation of the QTc interval. However, the degree of QT prolongation observed with both 45 mg and 75 mg (1.67 times the maximum recommended daily dose) doses of mirtazapine was not at a level generally considered to be clinically meaningful. During postmarketing use of mirtazapine, cases of QT prolongation, Torsades de Pointes, ventricular tachycardia, and sudden death, have been reported [see Adverse Reactions (6.1, 6.2)]. The majority of reports occurred in association with overdose or in patients with other risk factors for QT prolongation, including concomitant use of QTc-prolonging medicines [see Drug Interactions (7) and Overdosage (10)]. Exercise caution when REMERON/REMERONSolTab is prescribed in patients with known cardiovascular disease or family history of QT prolongation, and in concomitant use with other drugs thought to prolong the QTc interval.

5.6 Drug Reaction with Eosinophilia and Systemic Symptoms (DRESS)

Drug reaction with eosinophilia and systemic symptoms (DRESS) has been reported with postmarketing use of mirtazapine. DRESS may present with a cutaneous reaction (such as rash or exfoliative dermatitis), eosinophilia, fever, and/or lymphadenopathy with systemic complications such as hepatitis, nephritis, pneumonitis, myocarditis, and/or pericarditis. DRESS is sometimes fatal. Discontinue REMERON/REMERONSolTab immediately if DRESS is suspected and institute appropriate treatment [see Contraindications (4), Adverse Reactions (6.2)].

5.7 Increased Appetite and Weight Gain

In U.S. controlled clinical studies, appetite increase was reported in 17% of patients treated with REMERON, compared to 2% for placebo. In these same trials, weight gain of ≥7% of body weight was reported in 7.5% of patients treated with mirtazapine, compared to 0% for placebo. In a pool of premarketing U.S. clinical studies, including many patients for long-term, open-label treatment, 8% of patients receiving REMERON discontinued for weight gain.

In an 8-week-long pediatric clinical trial of doses between 15 to 45 mg/day, 49% of REMERON-treated pediatric patients had a weight gain of at least 7%, compared to 5.7% of placebo-treated patients. The safety and effectiveness of REMERON/REMERONSolTab in pediatric patients with MDD have not been established [see Use in Specific Populations (8.4)].

5.8 Somnolence

In U.S. controlled studies, somnolence was reported in 54% of patients treated with REMERON, compared to 18% for placebo. In these studies, somnolence resulted in discontinuation for 10.4% of REMERON-treated patients, compared to 2.2% for placebo. It is unclear whether tolerance develops to the somnolent effects of REMERON/REMERONSolTab. Because of the potentially significant effects of REMERON/REMERONSolTab on impairment of performance, caution patients about engaging in activities that require alertness, including operating hazardous machinery and motor vehicles, until they are reasonably certain that REMERON/REMERONSolTab does not affect them adversely. The concomitant use of benzodiazepines and alcohol with REMERON/REMERONSolTab should be avoided [see Drug Interactions (7)].

5.9 Activation of Mania or Hypomania

In patients with bipolar disorder, treating a depressive episode with REMERON/REMERONSolTab or another antidepressant may precipitate a mixed/manic episode. In controlled clinical trials, patients with bipolar disorder were generally excluded; however, symptoms of mania or hypomania were reported in 0.2% of patients treated with REMERON. Prior to initiating treatment with REMERON/REMERONSolTab, screen patients for any personal or family history of bipolar disorder, mania, or hypomania.

5.10 Seizures

REMERON/REMERONSolTab has not been systematically evaluated in patients with seizure disorders. In premarketing clinical trials, 1 seizure was reported among the 2796 U.S. and non-U.S. patients treated with REMERON. REMERON/REMERONSolTab should be prescribed with caution in patients with a seizure disorder.

5.11 Elevated Cholesterol and Triglycerides

In U.S. controlled studies, nonfasting cholesterol increases to ≥20% above the upper limits of normal were observed in 15% of patients treated with REMERON, compared to 7% for placebo. In these same studies, nonfasting triglyceride increases to ≥500 mg/dL were observed in 6% of patients treated with REMERON, compared to 3% for placebo.

5.12 Hyponatremia

Hyponatremia may occur as a result of treatment with serotonergic antidepressants, including REMERON/REMERONSolTab. Cases with serum sodium lower than 110 mmol/L have been reported.

Signs and symptoms of hyponatremia include headache, difficulty concentrating, memory impairment, confusion, weakness, and unsteadiness, which may lead to falls. Signs and symptoms associated with more severe or acute cases have included hallucination, syncope, seizure, coma, respiratory arrest, and death. In many cases, this hyponatremia appears to be the result of the syndrome of inappropriate antidiuretic hormone secretion (SIADH).

In patients with symptomatic hyponatremia, discontinue REMERON/REMERONSolTab and institute appropriate medical intervention. Elderly patients, patients taking diuretics, and those who are volume-depleted may be at greater risk of developing hyponatremia [see Use in Specific Populations (8.5)].

5.13 Transaminase Elevations

Clinically significant ALT (SGPT) elevations (≥3 times the upper limit of the normal range) were observed in 2.0% (8/424) of patients treated with REMERON in a pool of short-term, U.S. controlled trials, compared to 0.3% (1/328) of placebo patients. While some patients were discontinued for the ALT increases, in other cases, the enzyme levels returned to normal despite continued REMERON treatment. REMERON/REMERONSolTab should be used with caution in patients with impaired hepatic function [see Use in Specific Populations (8.6), Clinical Pharmacology (12.3)].

5.14 Discontinuation Syndrome

There have been reports of adverse reactions upon the discontinuation of REMERON/REMERONSolTab (particularly when abrupt), including but not limited to the following: dizziness, abnormal dreams, sensory disturbances (including paresthesia and electric shock sensations), agitation, anxiety, fatigue, confusion, headache, tremor, nausea, vomiting, and sweating, or other symptoms which may be of clinical significance.

A gradual reduction in the dosage, rather than an abrupt cessation, is recommended [see Dosage and Administration (2.6)].

5.15 Use in Patients with Concomitant Illness

REMERON/REMERONSolTab has not been systematically evaluated or used to any appreciable extent in patients with a recent history of myocardial infarction or other significant heart disease. REMERON was associated with significant orthostatic hypotension in early clinical pharmacology trials with normal volunteers. Orthostatic hypotension was infrequently observed in clinical trials with depressed patients [see Adverse Reactions (6.1)]. REMERON/REMERONSolTab should be used with caution in patients with known cardiovascular or cerebrovascular disease that could be exacerbated by hypotension (history of myocardial infarction, angina, or ischemic stroke) and conditions that would predispose patients to hypotension (dehydration, hypovolemia, and treatment with antihypertensive medication).

5.16 Risks in Patients with Phenylketonuria

Phenylalanine can be harmful to patients with phenylketonuria (PKU). REMERONSolTab contains phenylalanine, a component of aspartame. REMERONSolTab contains the following amount of phenylalanine: 2.6 mg in 15 mg orally disintegrating tablet, 5.2 mg in 30 mg orally disintegrating tablet, and 7.8 mg in 45 mg orally disintegrating tablet. Before prescribing REMERONSolTab to a patient with PKU, consider the combined daily amount of phenylalanine from all sources, including REMERONSolTab.

6 ADVERSE REACTIONS

The following adverse reactions are described in more detail in other sections of the prescribing information:

- Hypersensitivity [see Contraindications (4)]
- Suicidal Thoughts and Behaviors [see Warnings and Precautions (5.1)]
- Agranulocytosis [see Warnings and Precautions (5.2)]
- Serotonin Syndrome [see Contraindications (4), Warnings and Precautions (5.3), Drug Interactions (7)]
- Angle-Closure Glaucoma [see Warnings and Precautions (5.4)]
- QT Prolongation and Torsades de Pointes [see Warnings and Precautions (5.5)]
- Drug Reaction with Eosinophilia and Systemic Symptoms (DRESS) [see Warnings and Precautions (5.6)]
- Increased Appetite and Weight Gain [see Warnings and Precautions (5.7)]
- Somnolence [see Warnings and Precautions (5.8)]
- Activation of Mania or Hypomania [see Warnings and Precautions (5.9)]
- Seizures [see Warnings and Precautions (5.10)]
- Elevated Cholesterol and Triglycerides [see Warnings and Precautions (5.11)]
- Hyponatremia [see Warnings and Precautions (5.12)]
- Transaminase Elevations [see Warnings and Precautions (5.13)]
- Discontinuation Syndrome [see Warnings and Precautions (5.14)]
- Use in Patients with Concomitant Illness [see Warnings and Precautions (5.15)]

6.1 Clinical Trial Experience

Because clinical trials are conducted under widely varying conditions, adverse reaction rates observed in the clinical trials of a drug cannot be directly compared to rates in the clinical trials of another drug and may not reflect the rates observed in practice.

The data described below are from clinical trials in which REMERON/REMERONSolTab was administered to 2796 patients in phase 2 and 3 clinical studies. The trials consisted of double-blind controlled and open-label studies, inpatient and outpatient studies, fixed dose, and titration studies.

Adverse Reactions Leading to Discontinuation of Treatment

Approximately 16% of the 453 patients who received REMERON in U.S. 6-week placebo-controlled clinical trials discontinued treatment due to an adverse reaction, compared to 7% of the 361 placebo-treated patients in those studies. The most common reactions leading to discontinuation (≥1% and at a rate at least twice that of placebo) are included in Table 2.

Table 2: Adverse Reactions (≥1% and at least twice placebo) Leading to Discontinuation of REMERON in 6-Week Clinical Trials in Patients with MDD
 | REMERON (n=453) | Placebo (n=361)
Somnolence | 10.4% | 2.2%
Nausea | 1.5% | 0%

Common Adverse Reactions

The most common adverse reactions (≥5% and twice placebo) associated with the use of REMERON are listed in Table 3.

Table 3: Adverse Reactions (≥5% and twice placebo) in 6-Week U.S. Clinical Trials of REMERON in Patients with MDD
 | REMERON (n=453) | Placebo (n=361)
Somnolence | 54% | 18%
Increased Appetite | 17% | 2%
Weight Gain | 12% | 2%
Dizziness | 7% | 3%

Table 4 enumerates adverse reactions that occurred in ≥1% of REMERON-treated patients, and were more frequent than the placebo-treated patients, who participated in 6-week, U.S. placebo-controlled trials in which patients were dosed in a range of 5 to 60 mg/day. This table shows the percentage of patients in each group who had at least 1 episode of an adverse reaction at some time during their treatment.

Table 4: Adverse Reactions (≥1% and greater than placebo) in 6-Week U.S. Clinical Studies of Remeron in Patients with MDD
 | REMERON (n=453) | Placebo (n=361)
Body as a Whole
Asthenia | 8% | 5%
Flu Syndrome | 5% | 3%
Back Pain | 2% | 1%
Digestive System
Dry Mouth | 25% | 15%
Increased Appetite | 17% | 2%
Constipation | 13% | 7%
Metabolic and Nutritional Disorders
Weight Gain | 12% | 2%
Peripheral Edema | 2% | 1%
Edema | 1% | 0%
Musculoskeletal System
Myalgia | 2% | 1%
Nervous System
Somnolence | 54% | 18%
Dizziness | 7% | 3%
Abnormal Dreams | 4% | 1%
Thinking Abnormal | 3% | 1%
Tremor | 2% | 1%
Confusion | 2% | 0%
Respiratory System
Dyspnea | 1% | 0%
Urogenital System
Urinary Frequency | 2% | 1%

ECG Changes

The electrocardiograms for 338 patients who received REMERON and 261 patients who received placebo in 6-week, placebo-controlled trials were analyzed. REMERON was associated with a mean increase in heart rate of 3.4 bpm, compared to 0.8 bpm for placebo. The clinical significance of these changes is unknown.

Other Adverse Reactions Observed During the Premarketing Evaluation of REMERON

The following list does not include reactions: 1) already listed in previous tables or elsewhere in labeling, 2) for which a drug cause was remote, 3) which were so general or excessively specific so as to be uninformative, 4) which were not considered to have significant clinical implications, or 5) which occurred at a rate equal to or less than placebo.

Adverse reactions are categorized by body system according to the following definitions: frequent adverse reactions are those occurring in at least 1/100 patients; infrequent adverse reactions are those occurring in 1/100 to 1/1000 patients; rare adverse reactions are those occurring in fewer than 1/1000 patients.

Body as a Whole: frequent: malaise, abdominal pain, abdominal syndrome acute; infrequent: chills, fever, face edema, ulcer, photosensitivity reaction, neck rigidity, neck pain, abdomen enlarged; rare: cellulitis, chest pain substernal.

Cardiovascular System: frequent: hypertension, vasodilatation; infrequent: angina pectoris, myocardial infarction, bradycardia, ventricular extrasystoles, syncope, migraine, hypotension; rare: atrial arrhythmia, bigeminy, vascular headache, pulmonary embolus, cerebral ischemia, cardiomegaly, phlebitis, left heart failure.

Digestive System: frequent: vomiting, anorexia; infrequent: eructation, glossitis, cholecystitis, nausea and vomiting, gum hemorrhage, stomatitis, colitis, liver function tests abnormal; rare: tongue discoloration, ulcerative stomatitis, salivary gland enlargement, increased salivation, intestinal obstruction, pancreatitis, aphthous stomatitis, cirrhosis of liver, gastritis, gastroenteritis, oral moniliasis, tongue edema.

Endocrine System: rare: goiter, hypothyroidism.

Hemic and Lymphatic System: rare: lymphadenopathy, leukopenia, petechia, anemia, thrombocytopenia, lymphocytosis, pancytopenia.

Metabolic and Nutritional Disorders: frequent: thirst; infrequent: dehydration, weight loss; rare: gout, SGOT increased, healing abnormal, acid phosphatase increased, SGPT increased, diabetes mellitus, hyponatremia.

Musculoskeletal System: frequent: myasthenia, arthralgia; infrequent: arthritis, tenosynovitis; rare: pathologic fracture, osteoporosis fracture, bone pain, myositis, tendon rupture, arthrosis, bursitis.

Nervous System: frequent: hypesthesia, apathy, depression, hypokinesia, vertigo, twitching, agitation, anxiety, amnesia, hyperkinesia, paresthesia; infrequent: ataxia, delirium, delusions, depersonalization, dyskinesia, extrapyramidal syndrome, libido increased, coordination abnormal, dysarthria, hallucinations, manic reaction, neurosis, dystonia, hostility, reflexes increased, emotional lability, euphoria, paranoid reaction; rare: aphasia, nystagmus, akathisia (psychomotor restlessness), stupor, dementia, diplopia, drug dependence, paralysis, grand mal convulsion, hypotonia, myoclonus, psychotic depression, withdrawal syndrome, serotonin syndrome.

Respiratory System: frequent: cough increased, sinusitis; infrequent: epistaxis, bronchitis, asthma, pneumonia; rare: asphyxia, laryngitis, pneumothorax, hiccup.

Skin and Appendages: frequent: pruritus, rash; infrequent: acne, exfoliative dermatitis, dry skin, herpes simplex, alopecia; rare: urticaria, herpes zoster, skin hypertrophy, seborrhea, skin ulcer.

Special Senses: infrequent: eye pain, abnormality of accommodation, conjunctivitis, deafness, keratoconjunctivitis, lacrimation disorder, angle-closure glaucoma, hyperacusis, ear pain; rare: blepharitis, partial transitory deafness, otitis media, taste loss, parosmia.

Urogenital System: frequent: urinary tract infection; infrequent: kidney calculus, cystitis, dysuria, urinary incontinence, urinary retention, vaginitis, hematuria, breast pain, amenorrhea, dysmenorrhea, leukorrhea, impotence; rare: polyuria, urethritis, metrorrhagia, menorrhagia, abnormal ejaculation, breast engorgement, breast enlargement, urinary urgency.

6.2 Postmarketing Experience

The following adverse reactions have been identified during post-approval use of REMERON. Because these reactions are reported voluntarily from a population of uncertain size, it is not always possible to reliably estimate their frequency or establish a causal relationship to drug exposure.

Cardiac disorders: ventricular arrhythmia (Torsades de Pointes)

Endocrine disorders: hyperprolactinemia (and related symptoms, e.g., galactorrhea and gynecomastia)

Musculoskeletal and connective tissue disorders: increased creatine kinase blood levels and rhabdomyolysis

Psychiatric disorders: somnambulism (ambulation and other complex behaviors out of bed)

Reproductive system and breast disorders: priapism

Skin and subcutaneous tissue disorders: severe skin reactions, including DRESS, Stevens-Johnson syndrome, bullous dermatitis, erythema multiforme and toxic epidermal necrolysis

7 DRUG INTERACTIONS

Table 5 includes clinically important drug interactions with REMERON/REMERONSolTab [see Clinical Pharmacology (12.3)].

Table 5: Clinically Important Drug Interactions with REMERON/REMERONSolTab
Monoamine Oxidase Inhibitors (MAOIs)
Clinical Impact | The concomitant use of serotonergic drugs, including REMERON/REMERONSolTab, and MAOIs increases the risk of serotonin syndrome.
Intervention | REMERON/REMERONSolTab is contraindicated in patients taking MAOIs, including MAOIs such as linezolid or intravenous methylene blue [see Dosage and Administration (2.4), Contraindications (4), Warnings and Precautions (5.3)].
Examples | selegiline, tranylcypromine, isocarboxazid, phenelzine, linezolid, methylene blue
Other Serotonergic Drugs
Clinical Impact | The concomitant use of serotonergic drugs with REMERON/REMERONSolTab increases the risk of serotonin syndrome.
Intervention | Monitor patients for signs and symptoms of serotonin syndrome, particularly during treatment initiation and dosage increases. If serotonin syndrome occurs, consider discontinuation of REMERON/REMERONSolTab and/or concomitant serotonergic drugs [see Warnings and Precautions (5.3)].
Examples | SSRIs, SNRIs, triptans, tricyclic antidepressants, fentanyl, lithium, amphetamines, St. John's Wort, tramadol, tryptophan, buspirone
Strong CYP3A Inducers
Clinical Impact | The concomitant use of strong CYP3A inducers with REMERON/REMERONSolTab decreases the plasma concentration of mirtazapine [see Clinical Pharmacology (12.3)].
Intervention | Increase the dose of REMERON/REMERONSolTab if needed with concomitant CYP3A inducer use. Conversely, a decrease in dosage of REMERON/REMERONSolTab may be needed if the CYP3A inducer is discontinued [see Dosage and Administration (2.5)].
Examples | phenytoin, carbamazepine, rifampin
Strong CYP3A Inhibitors
Clinical Impact | The concomitant use of strong CYP3A inhibitors with REMERON/REMERONSolTab may increase the plasma concentration of mirtazapine [see Clinical Pharmacology (12.3)].
Intervention | Decrease the dose of REMERON/REMERONSolTab if needed with concomitant strong CYP3A inhibitor use. Conversely, an increase in dosage of REMERON/REMERONSolTab may be needed if the CYP3A inhibitor is discontinued [see Dosage and Administration (2.5)].
Examples | itraconazole, ritonavir, nefazodone
Cimetidine
Clinical Impact | The concomitant use of cimetidine, a CYP1A2, CYP2D6, and CYP3A inhibitor, with REMERON/REMERONSolTab may increase the plasma concentration of mirtazapine [see Clinical Pharmacology (12.3)].
Intervention | Decrease the dose of REMERON/REMERONSolTab if needed with concomitant cimetidine use. Conversely, an increase in dosage of REMERON/REMERONSolTab may be needed if cimetidine is discontinued [see Dosage and Administration (2.5)].
Benzodiazepines and Alcohol
Clinical Impact | The concomitant use of benzodiazepines or alcohol with REMERON/REMERONSolTab increases the impairment of cognitive and motor skills produced by REMERON/REMERONSolTab alone.
Intervention | Avoid concomitant use of benzodiazepines and alcohol with REMERON/REMERONSolTab [see Warnings and Precautions (5.8), Clinical Pharmacology (12.3)].
Examples | diazepam, alprazolam, alcohol
Drugs that Prolong QTc Interval
Clinical Impact | The concomitant use of other drugs which prolong the QTc interval with REMERON/REMERONSolTab, increase the risk of QT prolongation and/or ventricular arrhythmias (e.g., Torsades de Pointes).
Intervention | Use caution when using REMERON/REMERONSolTab concomitantly with drugs that prolong the QTc interval [see Warnings and Precautions (5.5), Clinical Pharmacology (12.3)].
Warfarin
Clinical Impact | The concomitant use of warfarin with REMERON/REMERONSolTab may result in an increase in INR [see Clinical Pharmacology (12.3)].
Intervention | Monitor INR during concomitant use of warfarin with REMERON/REMERONSolTab.

8 USE IN SPECIFIC POPULATIONS

8.1 Pregnancy

Pregnancy Exposure Registry

There is a pregnancy exposure registry that monitors pregnancy outcomes in women exposed to antidepressants during pregnancy. Healthcare providers are encouraged to register patients by calling the National Pregnancy Registry for Antidepressants at 1-844-405-6185 or visiting online at https://womensmentalhealth.org/clinical-and-research-programs/pregnancyregistry/antidepressants/.

Risk Summary

Prolonged experience with mirtazapine in pregnant women, based on published observational studies and postmarketing reports, has not reliably identified a drug-associated risk of major birth defects, miscarriage or adverse maternal or fetal outcomes. There are risks associated with untreated depression in pregnancy (see Clinical Considerations).

In animal reproduction studies, oral administration of mirtazapine to pregnant rats and rabbits during the period of organogenesis revealed no evidence of teratogenic effects up to 20 and 17 times the maximum recommended human dose (MRHD) of 45 mg, respectively, based on mg/m^2 body surface area. However, in rats, there was an increase in postimplantation loss at 20 times the MRHD based on mg/m^2 body surface area. Oral administration of mirtazapine to pregnant rats during pregnancy and lactation resulted in an increase in pup deaths and a decrease in pup birth weights at doses 20 times the MRHD based on mg/m^2 body surface area (see Data).

The estimated background risk of major birth defects and miscarriage for the indicated population is unknown. All pregnancies have a background risk of birth defect, loss, or other adverse outcomes. In the U.S. general population, the estimated background risk of major birth defects and miscarriage in clinically recognized pregnancies is 2 to 4% and 15 to 20%, respectively.

Clinical Considerations

Disease-Associated Maternal and/or Embryo/Fetal Risk

Women who discontinue antidepressants during pregnancy are more likely to experience a relapse of major depression than women who continue antidepressants. This finding is from a prospective, longitudinal study that followed 201 pregnant women with a history of major depressive disorder who were euthymic and taking antidepressants at the beginning of pregnancy. Consider the risk of untreated depression when discontinuing or changing treatment with antidepressant medication during pregnancy and postpartum.

Data

Animal Data

Mirtazapine was administered orally to pregnant rats and rabbits during the period of organogenesis at doses of 2.5, 15, and 100 mg/kg/day and 2.5, 10, and 40 mg/kg/day, respectively, which are up to 20 and 17 times the maximum recommended human dose (MRHD) of 45 mg based on mg/m^2 body surface area, respectively. No evidence of teratogenic effects was observed. However, in rats, there was an increase in postimplantation loss in dams treated with mirtazapine at 100 mg/kg/day which is 20 times the MRHD based on mg/m^2 body surface area. Oral administration of mirtazapine at doses of 2.5, 15, and 100 mg/kg/day to pregnant rats during pregnancy and lactation resulted in an increase in pup deaths during the first 3 days of lactation and a decrease in pup birth weights at 20 times the MRHD based on mg/m^2 body surface area. The cause of these deaths is not known. The no effect dose level is 3 times the MRHD based on mg/m^2 body surface area.

8.2 Lactation

Risk Summary

Data from published literature report the presence of mirtazapine in human milk at low levels with relative infant doses for mirtazapine ranging between 0.6 and 2.8% of the maternal weight-adjusted dose (see Data). No adverse effects on the breastfed infant have been reported in most cases of maternal use of mirtazapine. There are no data on the effects of mirtazapine on milk production.

The developmental and health benefits of breastfeeding should be considered along with the mother’s clinical need for mirtazapine and any potential adverse effects on the breastfed infant from mirtazapine or from the underlying maternal condition.

Data

In a published pooled analysis of 8 breastfeeding mother-infant pairs, the mean (min, max) total relative infant doses for mirtazapine and its desmethyl metabolite were 1.5% (0.6%, 2.8%) and 0.4% (0.1%, 0.7%) of the maternal weight-adjusted dose (median (min, max) dose of 38 mg (30 mg, 120 mg), respectively). No adverse drug effects were reported for any of the infants.

8.4 Pediatric Use

The safety and effectiveness of REMERON/REMERONSolTab have not been established in pediatric patients with MDD. Two placebo-controlled trials in 258 pediatric patients with MDD have been conducted with REMERON, and the data were insufficient to establish the safety and effectiveness of REMERON/REMERONSolTab in pediatric patients with MDD.

Antidepressants increased the risk of suicidal thoughts and behaviors in pediatric patients [see Boxed Warning and Warnings and Precautions (5.1)].

In an 8-week-long clinical trial in pediatric patients receiving doses between 15 to 45 mg per day, 49% of REMERON-treated patients had a weight gain of at least 7%, compared to 5.7% of placebo-treated patients. The mean increase in weight was 4 kg (2 kg SD) for REMERON-treated patients versus 1 kg (2 kg SD) for placebo-treated patients [see Warnings and Precautions (5.7)].

8.5 Geriatric Use

Approximately 190 patients ≥65 years of age participated in clinical studies with REMERON. REMERON/REMERONSolTab is known to be substantially excreted by the kidney (75%), and the risk of decreased clearance of this drug is greater in patients with impaired renal function. Pharmacokinetic studies revealed a decreased clearance of mirtazapine in the elderly [see Clinical Pharmacology (12.3)].

Sedating drugs, including REMERON/REMERONSolTab, may cause confusion and over-sedation in the elderly. Elderly patients may be at greater risk of developing hyponatremia. Caution is indicated when administering REMERON/REMERONSolTab to elderly patients [see Warnings and Precautions (5.12), (5.15) and Clinical Pharmacology (12.3)]. In general, dose selection for an elderly patient should be conservative, usually starting at the low end of the dosing range, reflecting the greater frequency of decreased hepatic, renal, or cardiac function, and of concomitant disease or other drug therapy.

8.6 Renal or Hepatic Impairment

The clearance of mirtazapine is reduced in patients with moderate to severe renal or hepatic impairment. Consequently, plasma mirtazapine levels may be increased in these patient groups, compared to levels observed in patients without renal or hepatic impairment. Dosage decrease may be necessary when administering REMERON/REMERONSolTab to patients with moderate to severe renal or hepatic impairment [see Warnings and Precautions (5.13), Use in Specific Populations (8.5), and Clinical Pharmacology (12.3)].

8.7 Patients with Phenylketonuria

REMERONSolTab contains phenylalanine, a component of aspartame. REMERONSolTab contains the following amount of phenylalanine: 2.6 mg in 15 mg orally disintegrating tablet, 5.2 mg in 30 mg orally disintegrating tablet, and 7.8 mg in 45 mg orally disintegrating tablet [see Warnings and Precautions (5.16)].

10 OVERDOSAGE

Human Experience

In premarketing clinical studies, there were reports of REMERON overdose alone or in combination with other pharmacological agents. Signs and symptoms reported in association with overdose included disorientation, drowsiness, impaired memory, and tachycardia.

Based on postmarketing reports, serious outcomes (including fatalities) may occur at dosages higher than the recommended doses, especially with mixed overdoses. In these cases, QT prolongation and Torsades de Pointes have also been reported [see Warnings and Precautions (5.5), Adverse Reactions (6.2), and Drug Interactions (7)].

Overdose Management

No specific antidotes for mirtazapine are known.

Contact Poison Control (1-800-222-1222) for the latest recommendations.

11 DESCRIPTION

REMERON and REMERONSolTab contain mirtazapine. Mirtazapine has a tetracyclic chemical structure and belongs to the piperazino-azepine group of compounds. It is designated 1,2,3,4,10,14b-hexahydro-2-methylpyrazino [2,1-a] pyrido [2,3-c][2] benzazepine and has the empirical formula of C17H19N3. Its molecular weight is 265.35. The structural formula is the following and it is the racemic mixture:

Mirtazapine is a white to creamy white crystalline powder which is practically insoluble in water.

REMERON is available for oral administration as scored film-coated tablets containing 15 or 30 mg of mirtazapine Each tablet contains the following inactive ingredients: colloidal silicon dioxide anhydrous, corn starch, ferric oxide (yellow), hydroxypropyl cellulose, hypromellose, magnesium stearate, lactose monohydrate, polyethylene glycol 8000, and titanium dioxide. The 30 mg tablets also contain ferric oxide (red).

REMERONSolTab is available for oral administration as an orally disintegrating tablet containing 15, 30, or 45 mg of mirtazapine. REMERONSolTab also contains the following inactive ingredients: aspartame, citric acid anhydrous fine granular, crospovidone, hypromellose, magnesium stearate, mannitol, granular mannitol 2080, microcrystalline cellulose, natural and artificial orange flavor, polymethacrylate (Eudragit E100), povidone, sodium bicarbonate, and sugar spheres (composed of starch and sucrose).

12 CLINICAL PHARMACOLOGY

12.1 Mechanism of Action

The mechanism of action of mirtazapine for the treatment of major depressive disorder, is unclear. However, its efficacy could be mediated through its activity as an antagonist at central presynaptic α2-adrenergic inhibitory autoreceptors and heteroreceptors and enhancing central noradrenergic and serotonergic activity.

12.2 Pharmacodynamics

In preclinical studies, mirtazapine acts as an antagonist at α2-adrenergic inhibitory autoreceptors and heteroreceptors and as an antagonist at serotonin 5-HT2 and 5-HT3 receptors. Mirtazapine has no significant affinity for the 5-HT1A and 5-HT1B receptors.

Mirtazapine also acts as an antagonist of histamine (H1) receptors, peripheral α1-adrenergic receptors, and muscarinic receptors. Actions at these receptors may explain some of the other clinical effects of mirtazapine (e.g., its prominent somnolent effects and orthostatic hypotension may be explained by its inhibition of histamine (H1) receptors and peripheral α1-adrenergic receptors, respectively).

Cardiac Electrophysiology

The effect of REMERON (mirtazapine) on QTc interval was assessed in healthy subjects. At a dose of 75 mg (1.67 times the maximum recommended dosage), REMERON does not prolong the QTc interval to a clinically meaningful extent.

12.3 Pharmacokinetics

Plasma levels of mirtazapine are linearly related to dose over a dose range of 15 to 80 mg (1.78 times the maximum recommended dose). Steady state plasma levels of mirtazapine are attained within 5 days, with about 50% accumulation (accumulation ratio=1.5). The (–) enantiomer has an elimination half-life that is approximately twice as long as the (+) enantiomer and therefore achieves plasma levels that are about 3 times as high as that of the (+) enantiomer.

Absorption

Mirtazapine has an absolute bioavailability of about 50% following oral administration. Peak plasma concentrations of mirtazapine are reached within about 2 hours post dose.

Food Effect

The presence of food in the stomach has a minimal effect on both the rate and extent of absorption.

Distribution

Mirtazapine is approximately 85% bound to plasma proteins over a concentration range of 0.01 to 10 mcg/mL.

Elimination

Mirtazapine has a half-life of about 20 to 40 hours following oral administration of REMERON or REMERONSolTab.

Metabolism

Mirtazapine is extensively metabolized after oral administration. Major pathways of bio-transformation are demethylation and hydroxylation followed by glucuronide conjugation. In vitro data from human liver microsomes indicate that CYP2D6 and CYP1A2 are involved in the formation of the 8-hydroxy metabolite of mirtazapine, whereas CYP3A is considered to be responsible for the formation of the N-desmethyl and N-oxide metabolite. Several unconjugated metabolites possess pharmacological activity but are present in the plasma at very low levels.

Excretion

Mirtazapine and its metabolites are eliminated predominantly (75%) via urine with 15% in feces.

Specific Populations

Geriatric Patients

Following oral administration of REMERON Tablets 20 mg/day for 7 days to subjects of varying ages (range 25 to 74 years old), oral clearance of mirtazapine was reduced in the elderly compared to the younger subjects. The clearance in elderly males was 40% lower compared to younger males, while the clearance was 10% lower in elderly females compared to younger females [see Warnings and Precautions (5.15), Use in Specific Populations (8.5)].

Male and Female Patients

The mean elimination half-life of mirtazapine after oral administration ranges from approximately 20 to 40 hours across age and gender subgroups, with females of all ages exhibiting significantly longer elimination half-lives than males (mean half-life of 37 hours for females vs. 26 hours for males).

Race

There have been no clinical studies to evaluate the effect of race on the pharmacokinetics of REMERON.

Patients with Renal Impairment

When compared to subjects with normal renal function, total body clearance of mirtazapine was reduced approximately 30% in renal impaired patients with GFR=11–39 mL/min/1.73 m^2 and approximately 50% in renal impaired patients with GFR=<10 mL/min/1.73 m^2) [see Warnings and Precautions (5.15), Use in Specific Populations (8.6)].

Patients with Hepatic Impairment

Following a single 15-mg oral dose of REMERON, the oral clearance of mirtazapine in patients with hepatic impairment was decreased by approximately 30%, compared to subjects with normal hepatic function [see Warnings and Precautions (5.13, 5.15), Use in Specific Populations (8.6)].

Drug Interactions Studies

Warfarin

Mirtazapine (30 mg daily) at steady state caused a statistically significant increase (0.2) in the International Normalized Ratio (INR) in subjects treated with warfarin [see Drug Interactions (7)].

QTc-Prolonging Drugs

The risk of QT prolongation and/or ventricular arrhythmias (e.g., Torsades de Pointes) may be increased with concomitant use of medicines which prolong the QTc interval (e.g., some antipsychotics and antibiotics) and in mirtazapine overdose [see Warnings and Precautions (5.5), Adverse Reactions (6.1, 6.2), Drug Interactions (7), and Overdosage (10)].

Phenytoin

In healthy male subjects (n=18), phenytoin (200 mg daily, at steady state) increased mirtazapine (30 mg daily, at steady state) clearance about 2-fold, resulting in a decrease in average plasma mirtazapine concentrations of 45% [see Drug Interactions (7)]. Mirtazapine did not significantly affect the pharmacokinetics of phenytoin.

Carbamazepine

In healthy male subjects (n=24), carbamazepine (400 mg twice a day, at steady state) increased mirtazapine (15 mg twice a day, at steady state) clearance about 2-fold, resulting in a decrease in average plasma mirtazapine concentrations of 60% [see Drug Interactions (7)].

Cimetidine

In healthy male subjects (n=12), when cimetidine, a weak inhibitor of CYP1A2, CYP2D6, and CYP3A4, given at 800 mg b.i.d. at steady state was coadministered with mirtazapine (30 mg daily) at steady state, the Area Under the Curve (AUC) of mirtazapine increased more than 50% [see Drug Interactions (7)]. Mirtazapine did not cause relevant changes in the pharmacokinetics of cimetidine.

Ketoconazole

In healthy male Caucasian subjects (n=24), coadministration of the strong CYP3A4 inhibitor ketoconazole (200 mg b.i.d. for 6.5 days) increased the peak plasma levels and the AUC of a single 30 mg dose of mirtazapine by approximately 40% and 50%, respectively [see Drug Interactions (7)].

Amitriptyline

In healthy, CYP2D6 extensive metabolizer patients (n=32), amitriptyline (75 mg daily), at steady state, did not cause relevant changes to the pharmacokinetics of steady state mirtazapine (30 mg daily); mirtazapine also did not cause relevant changes to the pharmacokinetics of amitriptyline.

Paroxetine

In healthy CYP2D6 extensive metabolizer subjects (n=24), mirtazapine (30 mg/day), at steady state, did not cause relevant changes in the pharmacokinetics of steady state paroxetine (40 mg/day), a CYP2D6 inhibitor.

Lithium

No relevant clinical effects or significant changes in pharmacokinetics have been observed in healthy male subjects on concurrent treatment with lithium 600 mg/day for 10 days at steady state and a single 30 mg dose of mirtazapine. The effects of higher doses of lithium on the pharmacokinetics of mirtazapine are unknown.

Risperidone

Mirtazapine (30 mg daily) at steady state did not influence the pharmacokinetics of risperidone (up to 3 mg twice a day) in subjects (n=6) in need of treatment with an antipsychotic and antidepressant drug.

Alcohol

Concomitant administration of alcohol (equivalent to 60 g) had a minimal effect on plasma levels of mirtazapine (15 mg) in 6 healthy male subjects. However, the impairment of cognitive and motor skills produced by REMERON were shown to be additive with those produced by alcohol.

Diazepam

Concomitant administration of diazepam (15 mg) had a minimal effect on plasma levels of mirtazapine (15 mg) in 12 healthy subjects. However, the impairment of motor skills produced by REMERON has been shown to be additive with those caused by diazepam.

13 NONCLINICAL TOXICOLOGY

13.1 Carcinogenesis, Mutagenesis, Impairment of Fertility

Carcinogenesis

Carcinogenicity studies were conducted with mirtazapine given in the diet at doses of 2, 20, and 200 mg/kg/day to mice and 2, 20, and 60 mg/kg/day to rats. The highest doses used are approximately 20 and 12 times the maximum recommended human dose (MRHD) of 45 mg/day, based on body surface area (mg/m^2) in mice and rats, respectively. There was an increased incidence of hepatocellular adenoma and carcinoma in male mice at the high dose. In rats, there was an increase in hepatocellular adenoma in females at the mid and high doses and in hepatocellular tumors and thyroid follicular adenoma/cystadenoma and carcinoma in males at the high dose.

Mutagenesis

Mirtazapine was not mutagenic or clastogenic and did not induce general DNA damage as determined in several genotoxicity tests: Ames test, in vitro gene mutation assay in Chinese hamster V 79 cells, in vitro sister chromatid exchange assay in cultured rabbit lymphocytes, in vivo bone marrow micronucleus test in rats, and unscheduled DNA synthesis assay in HeLa cells.

Impairment of Fertility

In a fertility study in rats, mirtazapine was given at doses up to 100 mg/kg [20 times the maximum recommended human dose (MRHD), based on body surface area (mg/m^2)]. Mating and conception were not affected by the drug, but estrous cycling was disrupted at doses that were 3 or more times the MRHD, and pre-implantation losses occurred at 20 times the MRHD.

14 CLINICAL STUDIES

The efficacy of REMERON as a treatment for major depressive disorder was established in 4 placebo-controlled, 6-week trials in adult outpatients meeting DSM-III criteria for major depressive disorder. Patients were titrated with REMERON from a dose range of 5 mg to 35 mg/day. The mean mirtazapine dose for patients who completed these 4 studies ranged from 21 to 32 mg/day. Overall, these studies demonstrated REMERON to be superior to placebo on at least 3 of the following 4 measures: 21-Item Hamilton Depression Rating Scale (HDRS) total score; HDRS Depressed Mood Item; CGI Severity score; and Montgomery and Asberg Depression Rating Scale (MADRS). Superiority of REMERON over placebo was also found for certain factors of the HDRS, including anxiety/somatization factor and sleep disturbance factor.

Examination of age and gender subsets of the population did not reveal any differential responsiveness on the basis of these subgroupings.

In a longer-term study, patients meeting (DSM-IV) criteria for major depressive disorder who had responded during an initial 8 to 12 weeks of acute treatment on REMERON were randomized to continuation of REMERON or placebo for up to 40 weeks of observation for relapse. Response during the open phase was defined as having achieved a HAM-D 17 total score of ≤8 and a CGI-Improvement score of 1 or 2 at 2 consecutive visits beginning with week 6 of the 8 to 12 weeks in the open-label phase of the study. Relapse during the double-blind phase was determined by the individual investigators. Patients receiving continued REMERON treatment experienced significantly lower relapse rates over the subsequent 40 weeks compared to those receiving placebo. This pattern was demonstrated in both male and female patients.

16 HOW SUPPLIED/STORAGE AND HANDLING

REMERON tablets are supplied as:

Tablet Strength | Tablet Color/Shape | Tablet Markings | Package Configuration | NDC Code
15 mg | Yellow, oval tablet | Scored with "MSD" debossed on one side and "T3Z" on other side, on both sides of score line | Bottle / 30 count | 78206-160-01
30 mg | Red-brown, oval tablet | Scored with "MSD" debossed on one side and "T5Z" on other side, on both sides of score line | Bottle / 30 count | 78206-161-01

Storage

Store at 20°C to 25°C (68°F to 77°F); excursions permitted to 15°C to 30°C (59°F to 86°F) [see USP Controlled Room Temperature]. Protect from light and moisture.

REMERONSolTab orally disintegrating tablets are supplied as:

Tablet Strength | Tablet Color/Shape | Tablet Markings | Package Configuration | NDC Code
15 mg | White, round tablet | "T1Z" debossed on one side. | Box of 5 × 6-unit dose blister packs/ 30 count | 78206-156-01
30 mg | White, round tablet | "T2Z" debossed on one side. | Box of 5 × 6-unit dose blister packs/30 count | 78206-158-01
45 mg | White, round tablet | "T4Z" debossed on one side | Box of 5 × 6-unit dose blister packs/30 count | 78206-159-01

Storage

Store at 20°C to 25°C (68°F to 77°F); excursions permitted to 15°C to 30°C (59°F to 86°F) [see USP Controlled Room Temperature]. Protect from light and moisture. Use immediately upon opening individual tablet blister.

17 PATIENT COUNSELING INFORMATION

Advise the patient to read the FDA-approved patient labeling (Medication Guide).

Suicidal Thoughts and Behaviors

Advise patients and caregivers to look for the emergence of suicidality, especially early during treatment and when the dosage is adjusted up or down, and instruct them to report such symptoms to the healthcare provider [see Boxed Warning and Warnings and Precautions (5.1)].

Agranulocytosis

Advise patients to contact their physician if they experience fever, chills, sore throat, mucous membrane ulceration, flu-like complaints, or other symptoms that might suggest infection [see Warnings and Precautions (5.2)].

Serotonin Syndrome

Caution patients about the risk of serotonin syndrome, particularly with the concomitant use of REMERON/REMERONSolTab with other serotonergic drugs including triptans, tricyclic antidepressants, fentanyl, lithium, tramadol, tryptophan, buspirone, amphetamines, St. John's Wort, and with drugs that impair metabolism of serotonin (in particular, MAOIs, both those intended to treat psychiatric disorders and also others, such as linezolid). Advise patients to contact their healthcare provider or report to the emergency room if they experience signs or symptoms of serotonin syndrome [see Dosage and Administration (2.4), Contraindications (4), Warnings and Precautions (5.3), Drug Interactions (7)].

QT Prolongation and Torsades de Pointes

Inform patients to consult their physician immediately if they feel faint, lose consciousness, or have heart palpitations [see Warnings and Precautions (5.5), Drug Interactions (7), Overdosage (10)]. Advise patients to inform physicians that they are taking REMERON/REMERONSolTab before any new drug is taken.

Drug Reaction with Eosinophilia and Systemic Symptoms (DRESS)

Advise patients to report to their healthcare provider at the earliest onset of fever, rash, swollen lymph nodes, or other signs and symptoms suggestive of Drug Reaction with Eosinophilia and Systemic Symptoms (DRESS) [see Contraindications (4), Warnings and Precautions (5.6)].

Somnolence

Advise patients that REMERON/REMERONSolTab may impair judgment, thinking, and particularly, motor skills, because of its prominent sedative effect. Caution patients about performing activities requiring mental alertness, such as operating hazardous machinery or operating a motor vehicle, until they are reasonably certain that REMERON/REMERONSolTab therapy does not adversely affect their ability to engage in such activities. [see Warnings and Precautions (5.8)].

Alcohol

Advise patients to avoid alcohol while taking REMERON/REMERONSolTab [see Warnings and Precautions (5.8), Drug Interactions (7)].

Activation of Mania/Hypomania

Advise patients and their caregivers to observe for signs of activation of mania/hypomania and instruct them to report such symptoms to the healthcare provider [see Warnings and Precautions (5.9)].

Discontinuation Syndrome

Advise patients not to abruptly discontinue REMERON/REMERONSolTab and to discuss any tapering regimen with their healthcare provider. Adverse reactions can occur when REMERON/REMERONSolTab is discontinued [see Dosage and Administration (2.6), Warnings and Precautions (5.14)].

Allergic Reactions

Advise patients to notify their healthcare provider if they develop an allergic reaction such as rash, hives, swelling, or difficulty breathing [see Contraindications (4), Adverse Reactions (6.2)].

Pregnancy

- Advise patients to notify their physician if they become pregnant or intend to become pregnant during REMERON/REMERONSolTab therapy.
- Advise patients that there is a pregnancy exposure registry that monitors pregnancy outcomes in women exposed to REMERON/REMERONSolTab during pregnancy [see Use in Specific Populations (8.1)].

Lactation

Advise patients to notify their physician if they are breastfeeding an infant [see Use in Specific Populations (8.2)].

Angle-Closure Glaucoma

Patients should be advised that taking REMERON can cause mild pupillary dilation, which in susceptible individuals, can lead to an episode of angle-closure glaucoma. Pre-existing glaucoma is almost always open-angle glaucoma because angle-closure glaucoma, when diagnosed, can be treated definitively with iridectomy. Open-angle glaucoma is not a risk factor for angle-closure glaucoma. Patients may wish to be examined to determine whether they are susceptible to angle-closure, and have a prophylactic procedure (e.g., iridectomy), if they are susceptible [see Warnings and Precautions (5.4).]

Patients with Phenylketonuria

Inform patients with phenylketonuria that REMERONSolTab contains phenylalanine [see Warnings and Precautions (5.16)].

Distributed by: Organon USA LLC, a subsidiary of
ORGANON & Co.,
Jersey City, NJ 07302, USA

For patent information: www.organon.com/our-solutions/patent/

© 2021 Organon group of companies. All rights reserved.

uspi-og8246-t-tod-2111r001

MEDICATION GUIDE
REMERON® (rĕm' - ĕ – rŏn)
(mirtazapine)
tablets, for oral use
REMERONSolTab® (rĕm' - ĕ - rŏn - sŏl' – tăb)
(mirtazapine)
orally disintegrating tablets, for oral use

What is the most important information I should know about REMERON and REMERONSolTab?

REMERON and REMERONSolTab may cause serious side effects, including:

- Increased risk of suicidal thoughts or actions in some children and young adults. REMERON, REMERONSolTab, and other antidepressant medicines may increase suicidal thoughts or actions in some people 24 years of age and younger, especially within the first few months of treatment or when the dose is changed. REMERON and REMERONSolTab are not for use in children.
  - Depression or other serious mental illnesses are the most important causes of suicidal thoughts or actions.
  How can I watch for and try to prevent suicidal thoughts and actions?
  - Pay close attention to any changes, especially sudden changes in mood, behavior, thoughts, or feelings, or if you develop suicidal thoughts or actions. This is very important when an antidepressant medicine is started or when the dose is changed.
  - Call your healthcare provider right away to report new or sudden changes in mood, behavior, thoughts, or feelings.
  - Keep all follow-up visits with your healthcare provider as scheduled. Call your healthcare provider between visits as needed, especially if you have concerns about symptoms.
  Call your healthcare provider or get emergency medical help right away if you or your family member have any of the following symptoms, especially if they are new, worse, or worry you:

- attempts to commit suicide
- acting aggressive, being angry or violent
- new or worse depression
- panic attacks
- new or worse irritability
- an extreme increase in activity or talking (mania)

- acting on dangerous impulses
- thoughts about suicide or dying
- new or worse anxiety
- feeling very agitated or restless
- trouble sleeping
- other unusual changes in behavior or mood

What is REMERON and REMERONSolTab?

REMERON and REMERONSolTab are prescription medicines used to treat a certain type of depression called Major Depressive Disorder (MDD) in adults.

It is not known if REMERON and REMERONSolTab are safe and effective for use to treat MDD in children.

Who should not take REMERON and REMERONSolTab?

Do not take REMERON or REMERONSolTab if you:

- take a Monoamine Oxidase Inhibitor (MAOI)
- have stopped taking an MAOI in the last 14 days
- are being treated with the antibiotic linezolid or intravenous methylene blue
- if you are allergic to mirtazapine or any of the ingredients in REMERON or REMERONSolTab. See the end of this Medication Guide for a complete list of ingredients in REMERON and REMERONSolTab.

Ask your healthcare provider or pharmacist if you are not sure if you take an MAOI, including the antibiotic linezolid or intravenous methylene blue.

Do not start taking an MAOI for at least 14 days after you stop treatment with REMERON or REMERONSolTab.

Before taking REMERON or REMERONSolTab, tell your healthcare provider about all your medical conditions, including if you:

- have a history of suicide or depression
- have a history or family history of bipolar disorder, mania or hypomania
- have a low white blood cell count
- have glaucoma (high pressure in the eye)
- have or had heart problems or stroke
- have an abnormal heart beat called QT prolongation or a family history of QT prolongation
- have seizures
- have high cholesterol or triglyceride levels
- have low sodium levels in your blood
- have or had kidney or liver problems
- have low blood pressure
- have phenylketonuria (PKU). REMERONSolTab contains phenylalanine which is a part of aspartame.
- are pregnant or plan to become pregnant. It is not known if REMERON and REMERONSolTab will harm your unborn baby.
  - Talk to your healthcare provider if you become pregnant or think you may be pregnant during treatment with REMERON and REMERONSolTab.
  - If you become pregnant while taking REMERON and REMERONSolTab, talk to your healthcare provider about registering with the National Pregnancy Registry for Antidepressants. You can register by calling 1-844-405-6185 or visiting online at https://womensmentalhealth.org/clinical-and-research-programs/pregnancyregistry/antidepressants/. The purpose of this registry is to monitor the pregnancy outcomes in women who have been treated with REMERON and REMERONSolTab at any time during pregnancy.
- are breastfeeding or plan to breastfeed. REMERON and REMERONSolTab may pass into your breast milk. Talk to your healthcare provider about the best way to feed your baby during treatment with REMERON and REMERONSolTab.

Tell your healthcare provider about all the medicines you take, including prescription and over-the-counter medicines, vitamins, and herbal supplements.

REMERON and REMERONSolTab and other medicines may affect each other causing possible serious side effects.

REMERON and REMERONSolTab may affect the way other medicines work and other medicines may affect the way REMERON and REMERONSolTab work.

Especially tell your healthcare provider if you take:

- MAOIs
- medicines to treat migraine headaches known as triptans
- tricyclic antidepressants
- fentanyl
- lithium
- tramadol
- tryptophan
- buspirone
- amphetamines
- benzodiazepines
- St. John's Wort
- medicines used to treat mood, anxiety, psychotic or thought disorders, including selective serotonin reuptake inhibitors (SSRIs) and serotonin norepinephrine reuptake inhibitors (SNRIs)
- medicines that may affect your heart rhythm (such as certain antibiotics and some antipsychotics)

Ask your healthcare provider if you are not sure if you are taking any of these medicines. Your healthcare provider can tell you if it is safe to take REMERON and REMERONSolTab with your other medicines.

Do not start or stop any other medicines during treatment with REMERON or REMERONSolTab without talking to your healthcare provider first. Stopping REMERON or REMERONSolTab suddenly may cause you to have serious side effects. See, "What are the possible side effects of REMERON and REMERONSolTab?"

Know the medicines you take. Keep a list of them to show to your healthcare provider and pharmacist when you get a new medicine.

How should I take REMERON or REMERONSolTab?

- Take REMERON and REMERONSolTab exactly as your healthcare provider tells you to. Do not change your dose or stop taking REMERON or REMERONSolTab without first talking to your healthcare provider.
- Your healthcare provider may need to change the dose of REMERON or REMERONSolTab until it is the right dose for you.
- Take REMERON or REMERONSolTab 1 time each day, preferably in the evening at bedtime.
- If you take too much REMERON or REMERONSolTab call your healthcare provider or poison control center at 1-800-222-1222 right away or go to the nearest hospital emergency room.

How to take REMERONSolTab:

- Keep REMERONSolTab in the blister pack until you are ready to take it. REMERONSolTab should be used immediately after opening the blister pack. Do not save it for future use.
- Use dry hands to open the blister pack.
- As soon as the blister pack is opened, remove REMERONSolTab right away and place it on the tongue.
- Place REMERONSolTab on the tongue and allow it to melt (disintegrate). Do not chew, crush, or split REMERONSolTab.
- REMERONSolTab will disintegrate rapidly on the tongue and can be swallowed with saliva. No water is needed for taking it.

What should I avoid while taking REMERON and REMERONSolTab?

- Do not drive, operate heavy machinery, or do other dangerous activities until you know how REMERON and REMERONSolTab affects you. REMERON and REMERONSolTab can cause sleepiness or may affect your ability to make decisions, think clearly, or react quickly.
- Avoid drinking alcohol during treatment with REMERON and REMERONSolTab.
- Avoid taking medicines used to treat anxiety, insomnia, and seizures, called benzodiazepines, during treatment with REMERON and REMERONSolTab. Ask your healthcare provider if you are not sure if you take one of these medicines.

What are the possible side effects of REMERON and REMERONSolTab?

REMERON and REMERONSolTab may cause serious side effects, including:

- See, "What is the most important information I should know about REMERON and REMERONSolTab?"
- Low white blood cell count. Tell your healthcare provider right away if you develop any signs or symptoms of a low white blood cell count, including:

- fever
- sore throat
- flu-like symptoms

- chills
- mouth or nose sores
- infections

- Serotonin syndrome. A potentially life-threatening problem called serotonin syndrome can happen when you take REMERON or REMERONSolTab with certain other medicines. See, "Who should not take REMERON and REMERONSolTab?" Stop taking REMERON or REMERONSolTab and call your healthcare provider or go to the nearest hospital emergency room right away if you have any of the following signs and symptoms of serotonin syndrome:

- agitation
- confusion
- fast heart beat
- dizziness
- flushing
- tremors, stiff muscles, or muscle twitching
- seizures

- seeing or hearing things that are not real (hallucinations)
- coma
- blood pressure changes
- sweating
- high body temperature (hyperthermia)
- loss of coordination
- nausea, vomiting, diarrhea

- Eye problems (angle-closure glaucoma). REMERON and REMERONSolTab may cause a certain type of eye problem called angle-closure glaucoma. Call your healthcare provider if you have eye pain, changes in your vision, or swelling or redness in or around the eye. Only some people are at risk for these problems. You may want to undergo an eye examination to see if you are at risk and receive preventative treatment if you are.
- Heart rhythm problems.
- Severe skin reaction. REMERON and REMERONSolTab may cause a severe skin reaction that may include rash, fever, swollen glands, and other organ involvement such as liver, kidney, lung and heart. The reaction may sometimes be fatal. Tell your healthcare provider right away if you experience any of these signs.
- Increased appetite and weight gain.
- Sleepiness. See, "What should I avoid while taking REMERON and REMERONSolTab?"
- Mania or hypomania (manic episodes) in people who have a history of bipolar disorder. Symptoms may include:

- greatly increased energy
- racing thoughts
- unusually grand ideas
- talking more or faster than usual

- severe trouble sleeping
- reckless behavior
- excessive happiness or irritability

- Seizures (convulsions).
- Increased fat levels (cholesterol and triglycerides) in your blood.
- Low sodium levels in your blood (hyponatremia). Low sodium levels in your blood may be serious and may cause death. Elderly people may be at greater risk for this. Signs and Symptoms of low sodium levels in your blood may include:

- headache
- memory changes
- weakness and unsteadiness on your feet which can lead to falls

- difficulty concentrating
- confusion

In severe or more sudden cases, signs and symptoms include:

- hallucinations (seeing or hearing things that are not real)
- seizures
- respiratory arrest

- fainting
- coma
- death

- Changes in liver function tests.
- Discontinuation syndrome. Suddenly stopping REMERON and REMERONSolTab may cause you to have serious side effects. Your healthcare provider may want to decrease your dose slowly. Symptoms may include:

- dizziness
- irritability and agitation
- anxiety
- sweating
- seizures
- ringing in your ears (tinnitus)

- nausea and vomiting
- problems sleeping
- tiredness
- confusion
- electric shock sensation (paresthesia)
- shaking (tremor)

- headache
- abnormal dreams
- changes in your mood
- hypomania

The most common side effects of REMERON and REMERONSolTab include:

- sleepiness
- increased appetite
- weight gain
- dizziness

These are not all the possible side effects of REMERON and REMERONSolTab.

Call your doctor for medical advice about side effects. You may report side effects to FDA at 1-800-FDA-1088.

How should I store REMERON and REMERONSolTab?

- Store REMERON and REMERONSolTab at room temperature between 68°F to 77°F (20°C to 25°C).
- Keep REMERON and REMERONSolTab away from light and moisture.

Keep REMERON, REMERONSolTab, and all medicines out of the reach of children.

General information about the safe and effective use of REMERON and REMERONSolTab.

Medicines are sometimes prescribed for purposes other than those listed in a Medication Guide. Do not use REMERON and REMERONSolTab for a condition for which it was not prescribed. Do not give REMERON and REMERONSolTab to other people, even if they have the same symptoms that you have. It may harm them. You can ask your healthcare provider or pharmacist for information about REMERON and REMERONSolTab that is written for healthcare professionals.

What are the ingredients in REMERON and REMERONSolTab?

Active ingredient: mirtazapine

Inactive ingredients:

REMERON Tablets: Colloidal silicon dioxide anhydrous, corn starch, ferric oxide (yellow), hydroxypropyl cellulose, hypromellose, polyethylene glycol 8000, lactose monohydrate, magnesium stearate, and titanium dioxide. The 30 mg tablets also contain ferric oxide (red).

REMERONSolTab: Aspartame, citric acid anhydrous fine granular, crospovidone, hypromellose, magnesium stearate, mannitol, granular mannitol 2080, microcrystalline cellulose, natural and artificial orange flavor, polymethacrylate (Eudragit E100), povidone, sodium bicarbonate, sugar spheres (made of starch and sucrose).

Distributed by: Organon USA LLC, a subsidiary of
ORGANON & Co.,
Jersey City, NJ 07302, USA

For patent information: www.organon.com/our-solutions/patent/
© 2021 Organon group of companies. All rights reserved.
For more information about REMERON/REMERONSolTab call 1-844-674-3200.

usmg-og8246-t-tod-2111r001

This Medication Guide has been approved by the U.S. Food and Drug Administration

Revised: 11/2021

PRINCIPAL DISPLAY PANEL - 15 mg Tablet Bottle Label

NDC 78206-160-01

REMERON®
(mirtazapine)Tablets

15 mg

Rx only

30 Tablets

Must be dispensed with Medication Guide.
Manuf. for: Organon USA LLC, a subsidiary of
ORGANON & Co.,
Jersey City, NJ 07302, USA
Manuf. by: Organon Pharma (UK) Limited
Cramlington, Northumberland, UK NE23 3JU
Mirtazapine (active ingred.) made in The Netherlands.
Formulated in UK.

PRINCIPAL DISPLAY PANEL - 30 mg Tablet Bottle Label

NDC 78206-161-01

REMERON®
(mirtazapine)Tablets

30 mg

Rx only

30 Tablets

Must be dispensed with Medication Guide.
Manuf. for: Organon USA LLC, a subsidiary of
ORGANON & Co.,
Jersey City, NJ 07302, USA
Manuf. by: Organon Pharma (UK) Limited
Cramlington, Northumberland, UK NE23 3JU
Mirtazapine (active ingred.) made in The Netherlands.
Formulated in UK.

PRINCIPAL DISPLAY PANEL - 15 mg Tablet Blister Pack Box

NDC 78206-156-01

30 Tablets

ONCE-A-DAY
REMERONSolTab®
(mirtazapine) Orally Disintegrating Tablets

Rx only

15 mg

Dispense the accompanying
Medication Guide to each patient.
Manufactured for: Organon USA LLC, a subsidiary of
ORGANON & Co.,
Jersey City, NJ 07302, USA

Manufactured by: Anesta LLC, Salt Lake City, UT 84116, USA

PRINCIPAL DISPLAY PANEL - 30 mg Tablet Blister Pack Box

NDC 78206-158-01

30 Tablets

ONCE-A-DAY
REMERONSolTab®
(mirtazapine) Orally Disintegrating Tablets

Rx only

30 mg

Dispense the accompanying Medication Guide to each patient.
Manufactured for: Organon USA LLC, a subsidiary of
ORGANON & Co.,
Jersey City, NJ 07302, USA

Manufactured by: Anesta LLC, Salt Lake City, UT 84116, USA

PRINCIPAL DISPLAY PANEL - 45 mg Tablet Blister Pack Box

NDC 78206-159-01

30 Tablets

ONCE-A-DAY
REMERONSolTab®
(mirtazapine) Orally Disintegrating Tablets

Rx only

45 mg

Dispense the accompanying Medication Guide to each patient.
Manufactured for: Organon USA LLC, a subsidiary of
ORGANON & Co.,
Jersey City, NJ 07302, USA

Manufactured by: Anesta LLC, Salt Lake City, UT 84116, USA